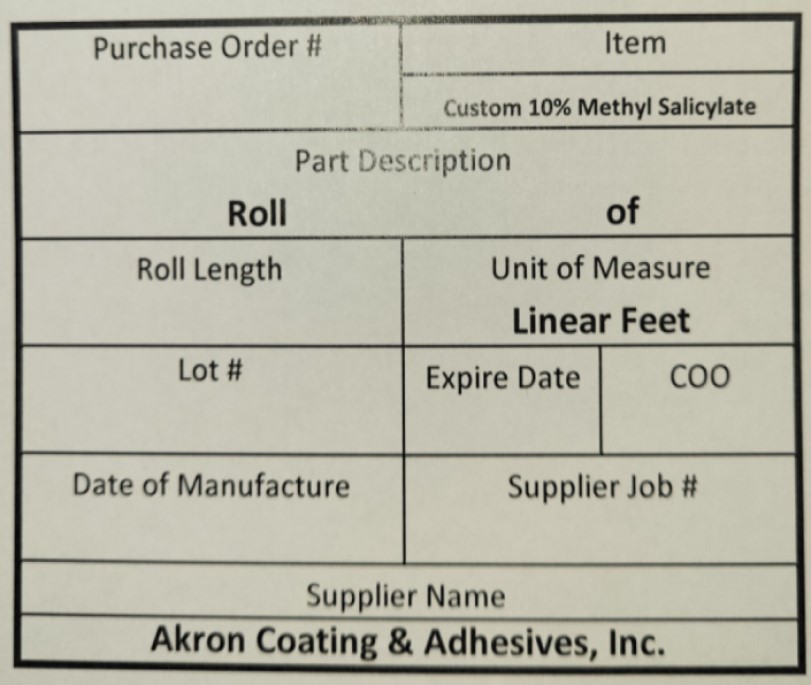 DRUG LABEL: 10% Methyl Salicylate Pain Relief Patch
NDC: 65604-222 | Form: TAPE
Manufacturer: Akron Coating & Adhesives
Category: otc | Type: HUMAN OTC DRUG LABEL
Date: 20240627

ACTIVE INGREDIENTS: METHYL SALICYLATE 10 mg/100 mg
INACTIVE INGREDIENTS: ETHYL ACRYLATE AND METHYL METHACRYLATE COPOLYMER (2:1; 600000 MW) 90 mg/100 mg

10 % Methyl Salicylate Pain relief patch

Purpose

Topical Anesthetic

Active Ingredient

10% Methyl Salicylate

Inactive ingredients

Acrylic Pressure Sensitive Adhesive

Uses

For the temporary relief of pain